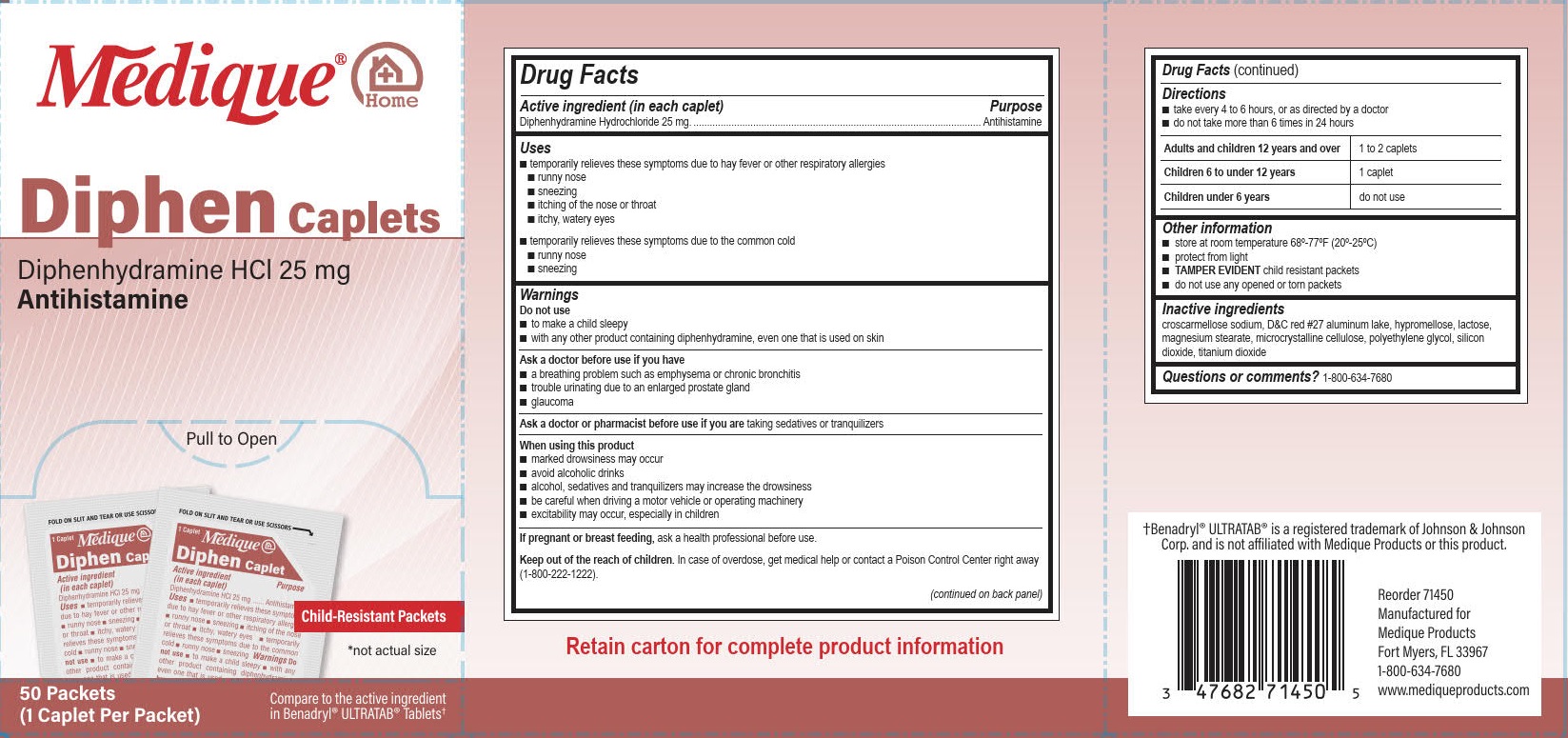 DRUG LABEL: Medique at Home Diphen
NDC: 47682-166 | Form: TABLET, FILM COATED
Manufacturer: Unifirst First Aid Corporation
Category: otc | Type: HUMAN OTC DRUG LABEL
Date: 20250908

ACTIVE INGREDIENTS: DIPHENHYDRAMINE HYDROCHLORIDE 25 mg/1 1
INACTIVE INGREDIENTS: POLYETHYLENE GLYCOL, UNSPECIFIED; CROSCARMELLOSE SODIUM; TITANIUM DIOXIDE; D&C RED NO. 27 ALUMINUM LAKE; MAGNESIUM STEARATE; CELLULOSE, MICROCRYSTALLINE; LACTOSE, UNSPECIFIED FORM; SILICON DIOXIDE; HYPROMELLOSE, UNSPECIFIED

Medique @ Home Diphen Caplet

Drug Facts

Active ingredient (in each caplet)

Diphenhydramine Hydrochloride 25 mg

Purpose

Antihistamine

Uses

■ temporarily relieves these symptoms due to hay fever or other respiratory allergies

■ runny nose ■ sneezing ■ itching of the nose or throat ■ itchy, watery eyes

■ temporarily relieves these symptoms due to the common cold

■ runny nose ■ sneezing

Warnings

Do not use

■ to make a child sleepy

■ with any other product containing diphenhydramine, even one that is used on skin.

Ask a doctor before use if you have

■ a breathing problem such as emphysema or chronic bronchitis

■ trouble urinating due to an enlarged prostate gland

■ glaucoma

Ask a doctor or pharmacist before use if you are taking sedatives or tranquilizers

When using this product

■ marked drowsiness may occur

■ avoid alcoholic drinks

■ alcohol, sedatives and tranquilizers may increase drowsiness

■ be careful when driving a motor vehicle or operating machinery

■ excitability may occur, especially in children

PREGNANCY OR BREAST FEEDING

If pregnant or breast feeding, ask a health professional before use.

KEEP OUT OF REACH OF CHILDREN

Keep out of the reach of children. In case of overdose, get medical help or contact a Poison Control Center right away (1-800-222-1222).

Directions

■ take every 4 to 6 hours, or as directed by a doctor

■ do not take more than 6 times in 24 hours

Adults and children12 years and over 1 to 2 caplets

Children 6 to under 12 years 1 caplet

Children under 6 years do not use

Other information

■ store at room temperature 68º-77ºF (20º-25ºC)

■ protect from light

■ TAMPER EVIDENT child resistant packets

■ do not use any opened or torn packets

Inactive ingredients

croscarmellose sodium, D&C red #27 aluminum lake, hypromellose, lactose, magnesium stearate, microcrystalline cellulose, polyethylene glycol, silicon dioxide, titanium dioxide

Questions or comments? 1-800-634-7680

PACKAGE LABEL

Medique® @ Home

Diphen Caplets

Diphenhydramine HCl 25 mg

Antihistamine

Pull to Open

Child-Resistant Packets

*not actual size

50 Packets

(1 Caplet Per Packet)

Compare to the active ingredient in Benadryl® Ultratab® Tablets